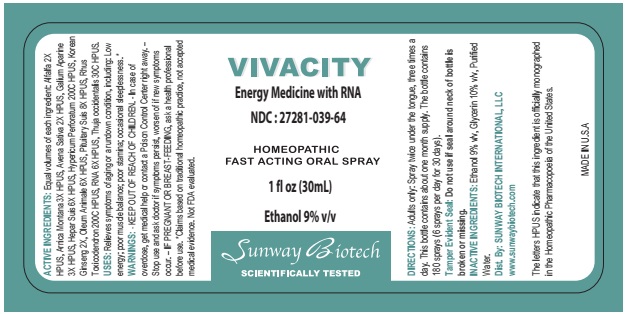 DRUG LABEL: VIVACITY
NDC: 27281-039 | Form: LIQUID
Manufacturer: Sunway Biotech LLC
Category: homeopathic | Type: HUMAN OTC DRUG LABEL
Date: 20211229

ACTIVE INGREDIENTS: ALFALFA 2 [hp_X]/30 mL; ARNICA MONTANA 3 [hp_X]/30 mL; AVENA SATIVA FLOWERING TOP 2 [hp_X]/30 mL; GALIUM APARINE 3 [hp_X]/30 mL; PORK LIVER 6 [hp_X]/30 mL; HYPERICUM PERFORATUM 200 [hp_C]/30 mL; ASIAN GINSENG 2 [hp_X]/30 mL; CERVUS ELAPHUS HORN OIL 6 [hp_X]/30 mL; SUS SCROFA PITUITARY GLAND 8 [hp_X]/30 mL; TOXICODENDRON PUBESCENS LEAF 200 [hp_C]/30 mL; SACCHAROMYCES CEREVISIAE RNA 6 [hp_X]/30 mL; THUJA OCCIDENTALIS LEAFY TWIG 30 [hp_C]/30 mL
INACTIVE INGREDIENTS: ALCOHOL; GLYCERIN; WATER

VIVACITY

ACTIVE INGREDIENT

ACTIVE INGREDIENTS: Equal volumes of each ingredient: Alfalfa 2X HPUS, Arnica Montana 3X HPUS, Avena Sativa 2X HPUS, Galium Aparine 3X HPUS, Hepar Suis6X HPUS, Hypericum Perforatum 200C HPUS, Korean Ginseng 2X, Oleum Animale 6X HPUS, Pituitary Suis 8X HPUS, Rhus Toxicodendron 200C HPUS, RNA 6X HPUS, Thuja occidentalis 30C HPUS.

The letters HPUS indicate that this ingredient is officially monographed in the Homeopathic Pharmacopoeia of the United States.

INDICATIONS AND USAGE

USES: Relieves symptoms of aging or a rundown condition, including: Low energy; poor muscle balance; poor stamina; occssional sleeplessnees.*

*Claims based on traditional homeopathic practice, not accepted by medical evidence. Not FDA evaluated.

WARNINGS

WARNINGS: KEEP OUT OF REACH OF CHILDREN. - In case of

overdose, get medical help or contact a Poison Control Center right away. -

Stop use and ask doctor if symptoms persist, worsen of if new symptoms occur. - IF PREGNANT OR BREAST -FEEDING, ask a health professional before use.

KEEP OUT OF REACH OF CHILDREN.

DOSAGE AND ADMINISTRATION

DIRECTIONS: Adults only: Spray twice under the tongues, three times a day. This bottle contains about one month supply. The bottle contains 180 sprays (6 sprays per day for 30 days).

OTHER SAFETY INFORMATION

Tamper Evident Seal: Do not use if seal around neck of bottle is broken or missing.

INACTIVE INGREDIENT

INACTIVE INGREDIENTS: Ethanol 9% v/v, Glycerin 10% v/v, Purified Water.

QUESTIONS

Dist. By: SUNWAY BIOTECH INTERNATIONAL, LLC

www.sunwaybiotech.com

PACKAGE LABEL

VIVACITY

Energy Medicine with RNA

NDC:27281-039-64

HOMEOPATHIC

FAST ACTING ORAL SPRAY

1 fl oz (30mL)

Ethanol 9% v/v

Sunway Biotech

SCIENTIFICALLY TESTED

MADE IN U.S.A

PURPOSE

Energy Medicine with RNA